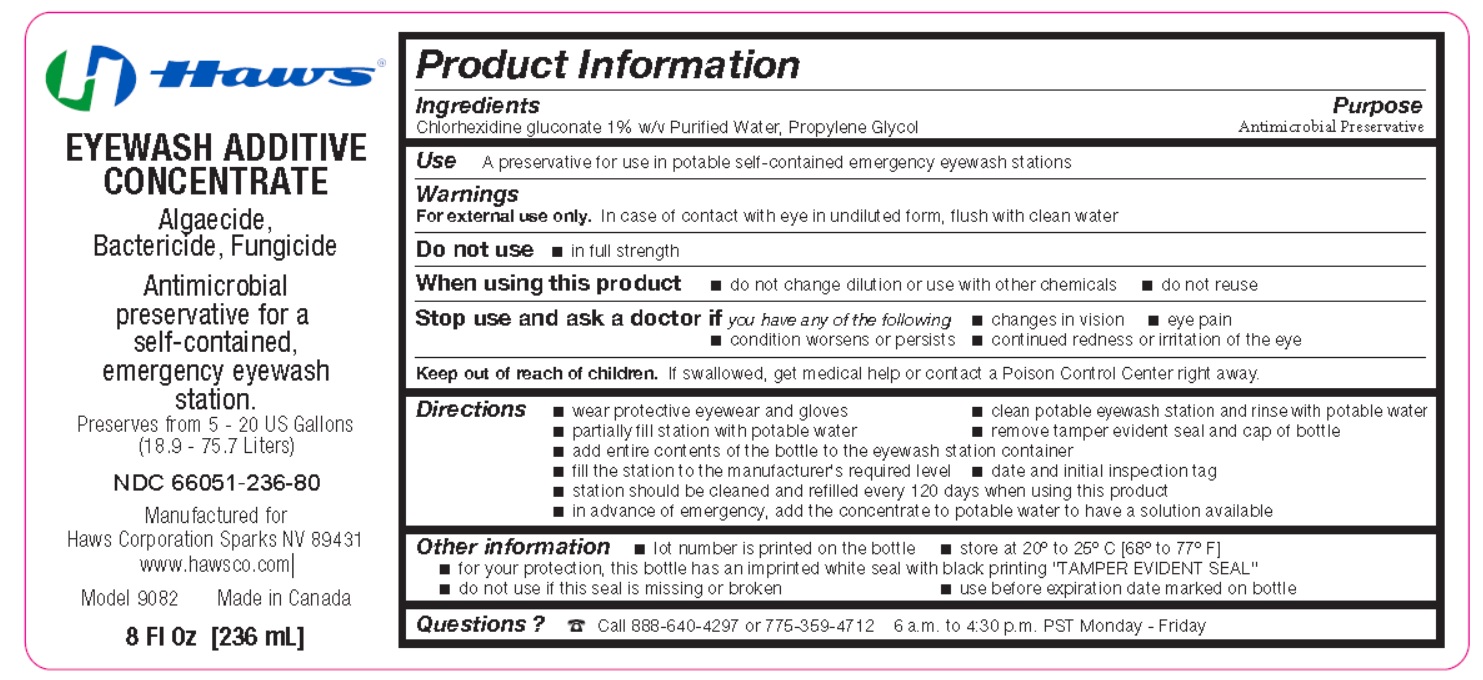 DRUG LABEL: Eyewash Additive Concentrate
NDC: 66051-236 | Form: LIQUID
Manufacturer: Haws Corporation
Category: otc | Type: HUMAN OTC DRUG LABEL
Date: 20251120

ACTIVE INGREDIENTS: WATER 2374.4 L/2800 L; PROPYLENE GLYCOL 280 kg/2800 L
INACTIVE INGREDIENTS: CHLORHEXIDINE GLUCONATE 145.6 kg/2800 L

EYEWASH ADDITIVE CONCENTRATE

Active Ingredient

Propylene Glycol, Water

Purpose

Antimicrobial Preservative

Use

A preservative for use in potable self-contained emergency eyewash stations

Warnings

For external use only.In case of contact with eye in undiluted form, flush with clean water

Do not use

- In full strength

When using this product

- do not change dilution or use with other chemicals
- do not reuse

Stop use and ask a doctor if you have any of the following

- changes in vision
- eye pain
- condition worsens or persists
- continued redness or irritation of the eye

Keep out of reach of children.

If swallowed, get medical help or contact a Poison Control Center right away.

Directions

- wear protective eyewear and gloves
- clean potable eyewash station and rinse with potable water
- partially fill station with potable water
- remove tamper evident seal and cap of bottle
- add entire contents of the bottle to the eyewash station container
- fill the station to the manufacturer’s required level
- date and initial inspection tag
- station should be cleaned and refilled every 120 days when using this product
- in advance of emergency, add the concentrate to potable water to have a solution available

Inactive ingredient

Chlorhexidine gluconate

Other information

- lot number is printed on the bottle
- store at 20° to 25° C [68° to 77° F]
- for your protection, this bottle has an imprinted white seal with black printing "TAMPER EVIDENT SEAL"
- do not use if this seal is missing or broken
- use before expiration date marked on bottle

Questions ?

☎ Call 888-640-4297 or 775-359-4712 6 a.m. to 4.30 p.m. PST Monday-Friday

PRINCIPAL DISPLAY PANEL

HAWS

NDC 66051-236-80

EYEWASH ADDITIVE CONCENTRATE

Algaecide, Bactericide, Fungicide

Antimicrobial preservative for a self-contained, emergency eyewash station.

Preserves from 5 - 20 US Gallons
(18.9 - 75.7 Liters)
Manufactured for
Haws Corporation Sparks NV 89431
www.hawsco.com

Model 9082

Made in Canada

8 Fl Oz [236 mL]